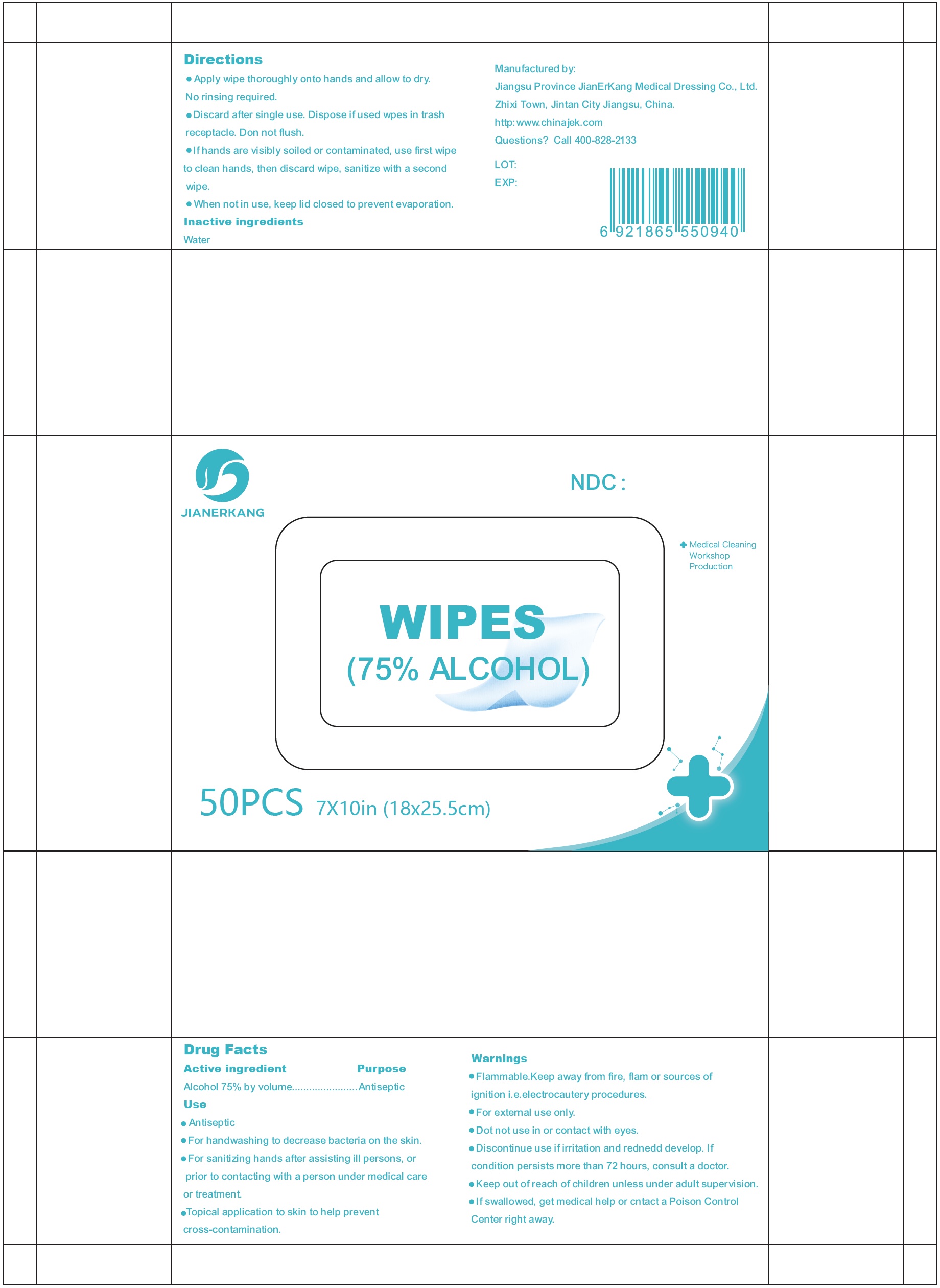 DRUG LABEL: Jianerkang Wipes
NDC: 34645-0004 | Form: CLOTH
Manufacturer: Jianerkang Medical Co., Ltd
Category: otc | Type: HUMAN OTC DRUG LABEL
Date: 20231023

ACTIVE INGREDIENTS: ALCOHOL 0.75 mL/1 mL
INACTIVE INGREDIENTS: WATER

Jianerkang Wipes, 50 pcs

Active Ingredient

Alcohol 75% by volume

Purpose

Antiseptic

Use

- Antiseptic
- For handwashing to decrease bacteria on the skin.
- For sanitizing hands after ill persons, or prior to contacting with a person under medical care treatment.
- Topical application to skin to help prevent cross-contamination.

Warnings

- Flammable. Keep away from fire, flame or sources of ignition. i.e. electrocautery procedures.
- For external use only.

- Do not use in or contact with eyes.

STOP USE

- Discontinue use if irritation and redness develop. If condition persists more than 72 hours, consult a doctor.

- Keep out of reach of children unless under adult supervision.
- If swallowed, get medical help or contact a Poison Control Center right away.

Directions

- Apply wipe thoroughly onto hands and allow to dry. No rinsing required.
- Discard after single use. Dispose if used wpes in trash receptacle. Don not flush.
- If hands are visibly soiled or contaminated, use first wipe to clean hands, then discard wipe, sanitize with a second wipe.
- When not in use, keep lid closed to prevent evaporation.

Inactive Ingredients

Water

Questions? Call 400-828-2133